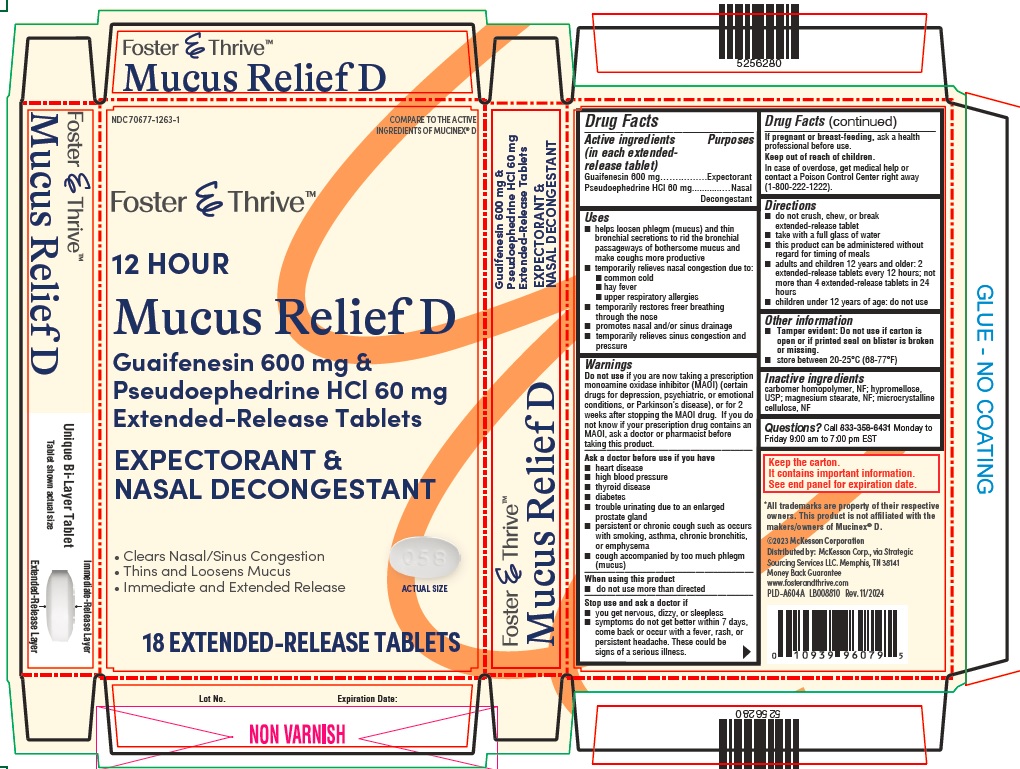 DRUG LABEL: Guaifenesin and Pseudoephedrine HCl
NDC: 70677-1263 | Form: TABLET, EXTENDED RELEASE
Manufacturer: Strategic Sourcing Services LLC
Category: otc | Type: HUMAN OTC DRUG LABEL
Date: 20241128

ACTIVE INGREDIENTS: GUAIFENESIN 600 mg/1 1; PSEUDOEPHEDRINE HYDROCHLORIDE 60 mg/1 1
INACTIVE INGREDIENTS: CARBOMER HOMOPOLYMER TYPE B (ALLYL PENTAERYTHRITOL CROSSLINKED); MAGNESIUM STEARATE; HYPROMELLOSE 2910 (10000 MPA.S); MICROCRYSTALLINE CELLULOSE

Drug Facts

ACTIVE INGREDIENT

PURPOSE

Active ingredients (in each extended-release tablet) | Purposes
Guaifenesin 600 mg | Expectorant
Pseudoephedrine HCl 60 mg | Nasal Decongestant

Uses

- helps loosen phlegm (mucus) and thin bronchial secretions to rid the bronchial passageways of bothersome mucus and make coughs more productive
- temporarily relieves nasal congestion due to:
  - common cold
  - hay fever
  - upper respiratory allergies
- temporarily restores freer breathing through the nose
- promotes nasal and/or sinus drainage
- temporarily relieves sinus congestion and pressure

Warnings

Do not useif you are now taking a prescription monoamine oxidase inhibitor (MAOI) (certain drugs for depression, psychiatric or emotional conditions, or Parkinson’s disease), or for 2 weeks after stopping the MAOI drug. If you do not know if your prescription drug contains an MAOI, ask a doctor or pharmacist before taking this product.

Ask a doctor before use if you have

- heart disease
- high blood pressure
- thyroid disease
- diabetes
- trouble urinating due to an enlarged prostate gland
- persistent or chronic cough such as occurs with smoking, asthma, chronic bronchitis, or emphysema
- cough accompanied by too much phlegm (mucus)

When using this product

- do not use more than directed

Stop use and ask a doctor if

- you get nervous, dizzy, or sleepless
- symptoms do not get better within 7 days, come back or occur with a fever, rash, or persistent headache. These could be signs of a serious illness.

If pregnant or breast-feeding, ask a health professional before use.

Directions

- do not crush, chew, or break extended-release tablet
- take with a full glass of water
- this product can be administered without regard for timing of meals
- adults and children 12 years and older: 2 extended-release tablets every 12 hours; not more than 4 extended-release tablets in 24 hours
- children under 12 years of age: do not use

Other Information

- Tamper evident: Do not use if carton is open or if printed seal on blister is broken or missing.
- store between 20-25°C (68-77°F)

Inactive Ingredients

carbomer homopolymer, NF; hypromellose, USP; magnesium stearate, NF; microcrystalline cellulose, NF

Questions?

Call 833-358-6431 Monday to Friday 9:00 am to 7:00 pm EST

Keep the carton. It contains important information.

See end panel for expiration date.

*All trademarks are property of their respective owners. This product is not affliated with the makers/owners of Mucinex® D.

©2023 McKesson Corporation

Distributed by: McKesson Corp.,

via Strategic Sourcing Services LLC.

Memphis, TN 38141
Money Back Guarantee
www.fosterandthrive.com
Rev. 11/2024

Guaifenesin 600 mg and Pseudoephedrine HCl 60 mg Extended-Release Tablets - Carton Label

NDC 70677-1263-1

COMPARE TO THE ACTIVE

INGREDIENTS OF MUCINEX ®D

Foster & ThriveTM

12 HOUR

Mucus Relief D

Guaifenesin 600 mg & Pseudoephedrine HCl 60 mg
Extended-Release Tablets

EXPECTORANT & NASAL DECONGESTANT

- Clears Nasal/Sinus Congestion
- Thins and Loosens Mucus
- Immediate and Extended Release

ACTUAL SIZE

18 EXTENDED-RELEASE TABLETS